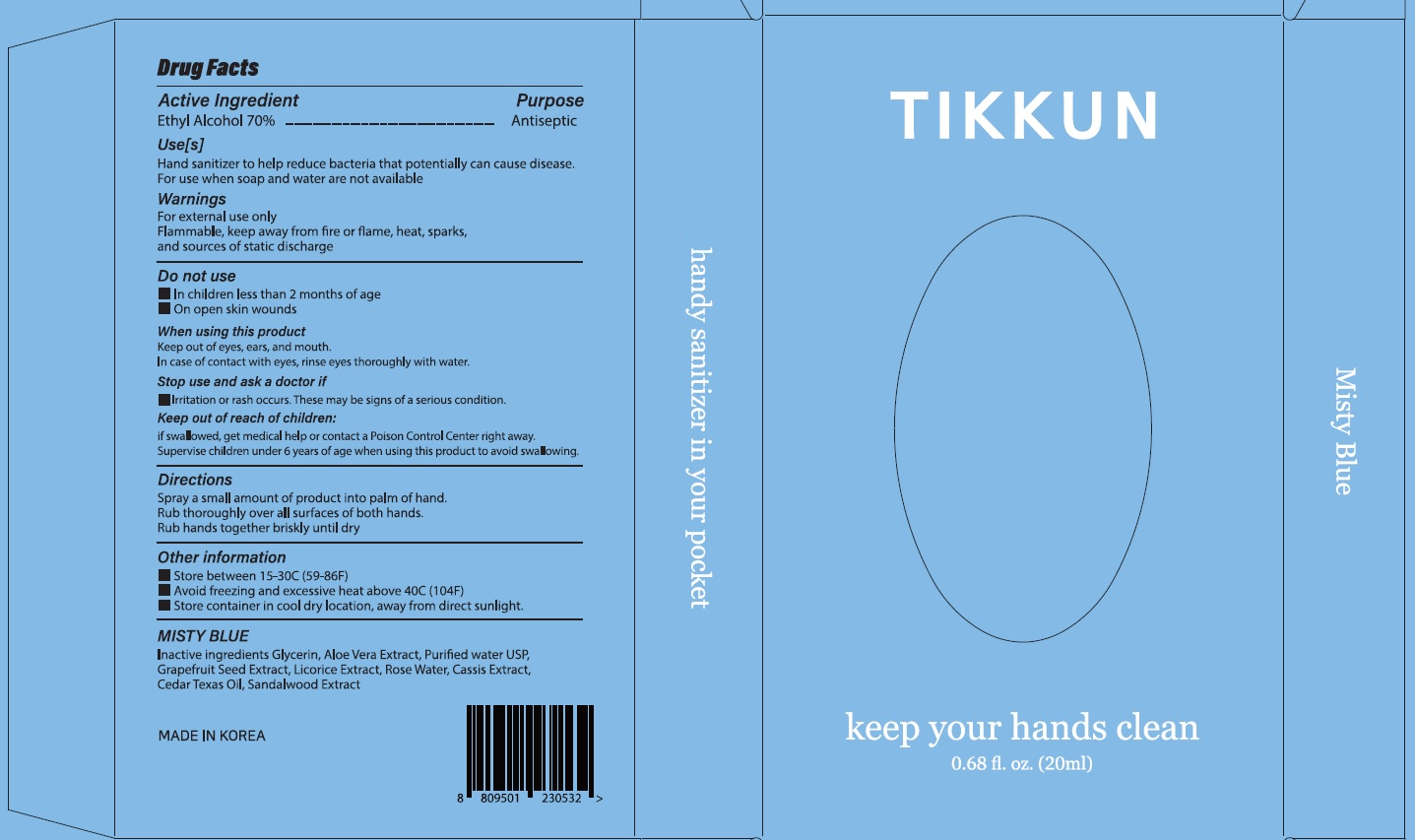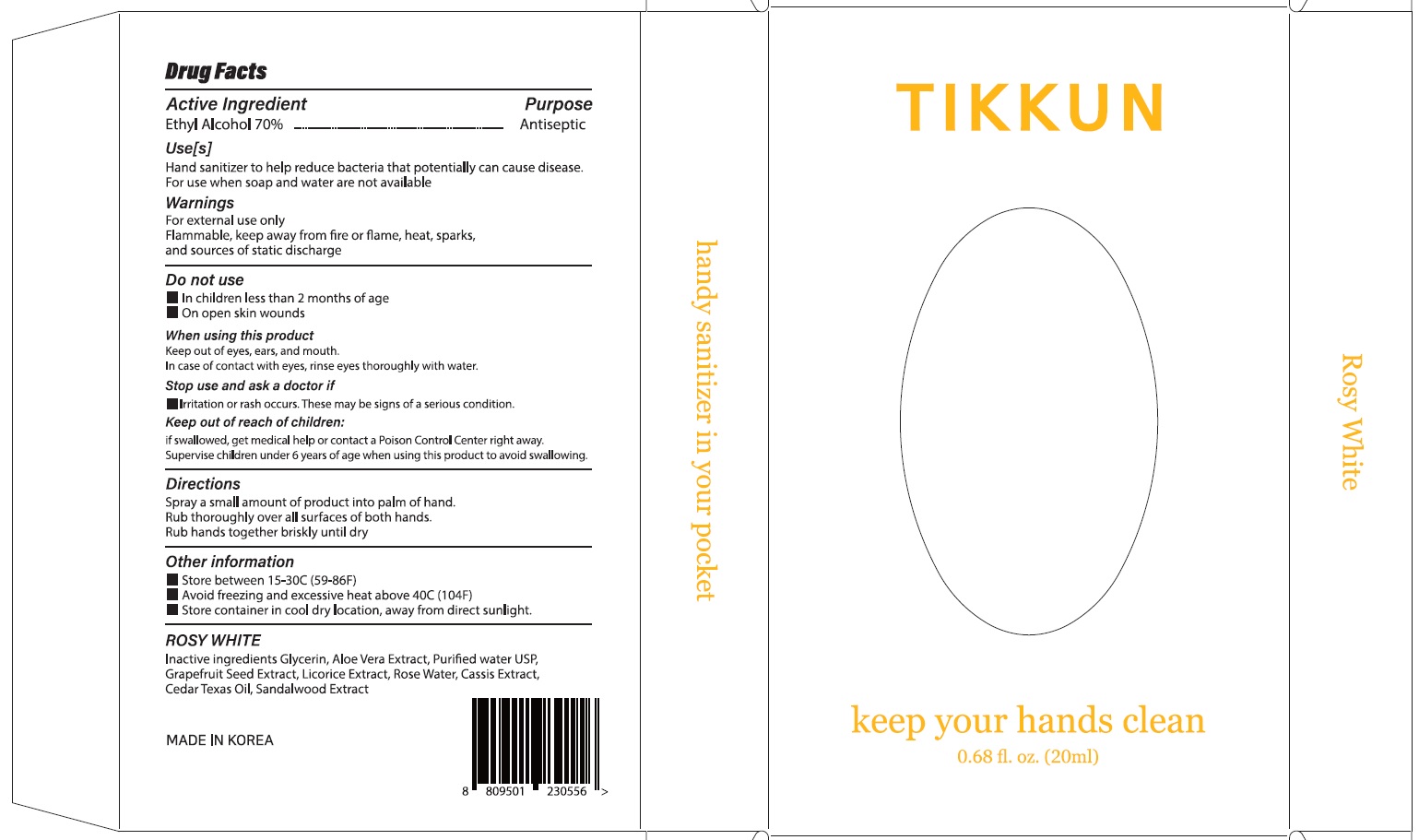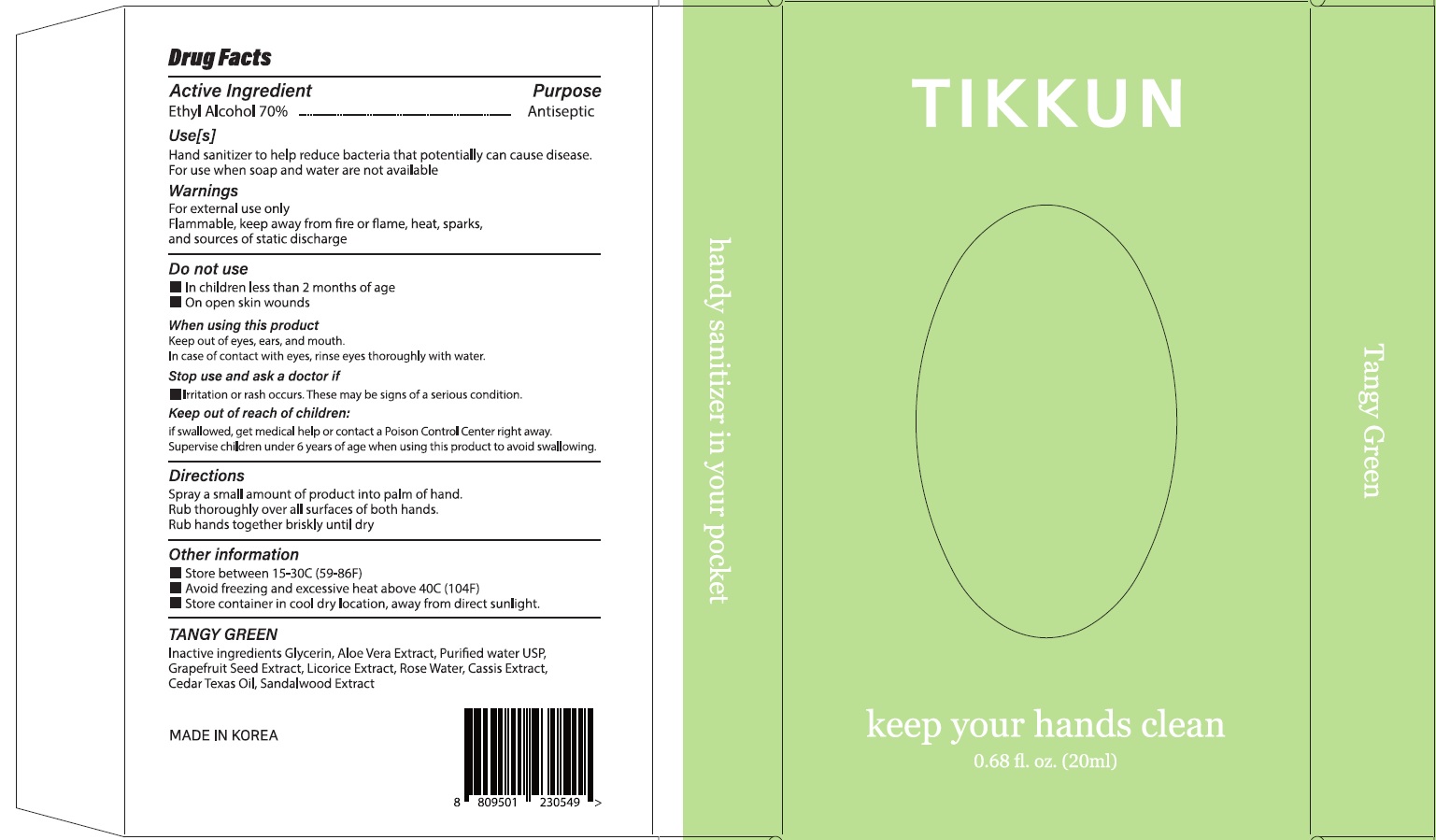 DRUG LABEL: TIKKUN Hand Sanitizer
NDC: 74923-130 | Form: SPRAY
Manufacturer: THE SUN CO.LTD
Category: otc | Type: HUMAN OTC DRUG LABEL
Date: 20210316

ACTIVE INGREDIENTS: Alcohol 14 mL/20 mL
INACTIVE INGREDIENTS: Water; Glycerin; ALOE VERA LEAF; CITRUS PARADISI SEED; LICORICE; SANDALWOOD

ACTIVE INGREDIENT

Ethyl Alcohol 70.0%

INACTIVE INGREDIENTS

Glycerin, Aloe Vera Extract, Purified Water USP, Grapefruit Seed Extract, Licorice Extract, Rose Water, Cassis Extract, Cedar Texas Oil, Sandalwood Extract

PURPOSE

Antiseptic

WARNINGS

For external use only
Flammable. Keep away from heat and flame, heat, sparks, and sources of static discharge

Do not use

■ In children less than 2 months of age

■ On open skin wounds

When using this product
■ Keep out of eyes, ears and mouth.
■ In case of contact with eyes, rinse thoroughly with water

Stop use and ask a doctor if

■ irritation or rash occurs. These may be signs of a serious condition.

KEEP OUT OF REACH OF CHILDREN

If swallowed, get medical help or contact a Poison Control Center right away.

Supervise children under 6 years of age when using this product to avoid swallowing

Use[s]

Hand sanitizer to help reduce bacteria that potentially can cause disease.

For use when soap and water are not available.

Directions

Spray a small amount of product into palm of hand.

Rub thoroughly over all surfaces of both hands

Rub hands together briskly until dry

Other Information

■ Store between 15-30C(59-86F)
■ Avoid freezing and excessive heat above 40C(104F)
■ Store container in cool dry location, away from direct sunlight